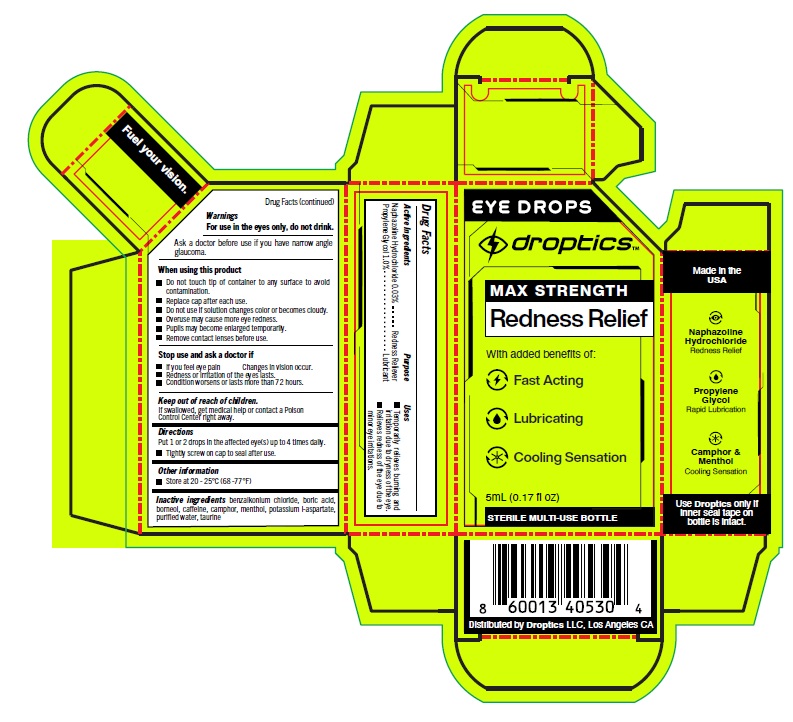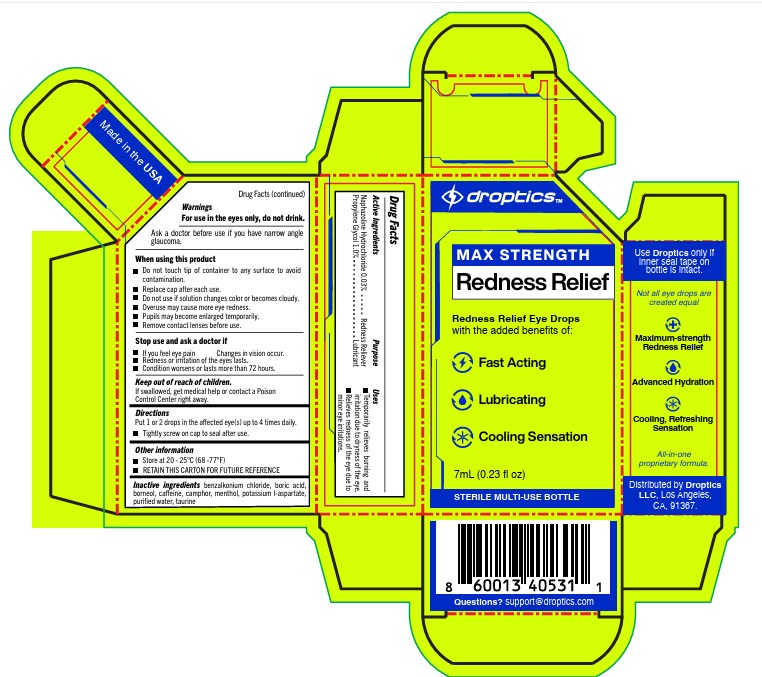 DRUG LABEL: Droptics Performance Eye Drops
NDC: 85211-001 | Form: LIQUID
Manufacturer: Droptics LLC
Category: otc | Type: HUMAN OTC DRUG LABEL
Date: 20260209

ACTIVE INGREDIENTS: NAPHAZOLINE HYDROCHLORIDE 0.03 g/100 mL; PROPYLENE GLYCOL 1 g/100 mL
INACTIVE INGREDIENTS: BENZALKONIUM CHLORIDE; BORIC ACID; BORNEOL; CAFFEINE; CAMPHOR (SYNTHETIC); MENTHOL; POTASSIUM ASPARTATE; WATER; TAURINE

Active Ingredients

Naphozoline Hydrochloride 0.03%
Propylene Glycol: 1.0%

Purpose

Redness Reliver
Lubricant

Uses

Temporarily relieves burning and irritation due to dryness of the eye
Relieves redness of the eye due to minor eye irritations

Warnings

For external use only
Ask a doctor before use if you have narrow angle glaucoma
When using this product
• Do not touch tip of container to any surface to avoid contamination
• Replace each cap after each use
• Do not use if solution changes color or becomes cloudy
• Overuse may cause more eye redness
• Pupils may become enlarged temporarily
• Remove contact lenses before use
Stop Use and ask a doctor if
• You feel eye pain
• Changes in vision occur
• Redness or irritation of the eyes lasts
• Condition worsens or lasts more than 72 hours
Keep out of reach of children
• If swallowed, get medical help or contact a Poison Control center right away

Directions

Put 1 or 2 drops in the affected eye(s) up to 4 times daily

- Tightly screw on cap to seal after use

Other information

Store at 20 - 25°C (68 -77°F)

Inactive ingredients

benzalkonium chloride, boric acid, borneol, caffeine, camphor, menthol, potassium l-aspartate, purified water, taurine